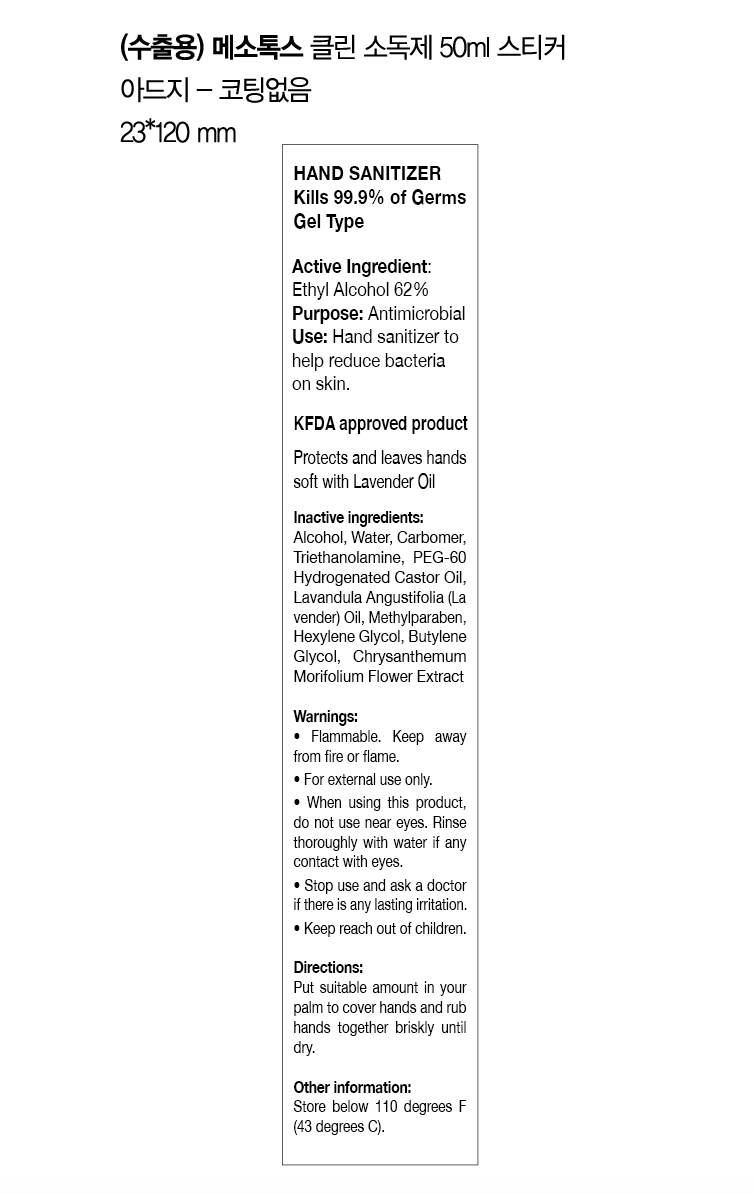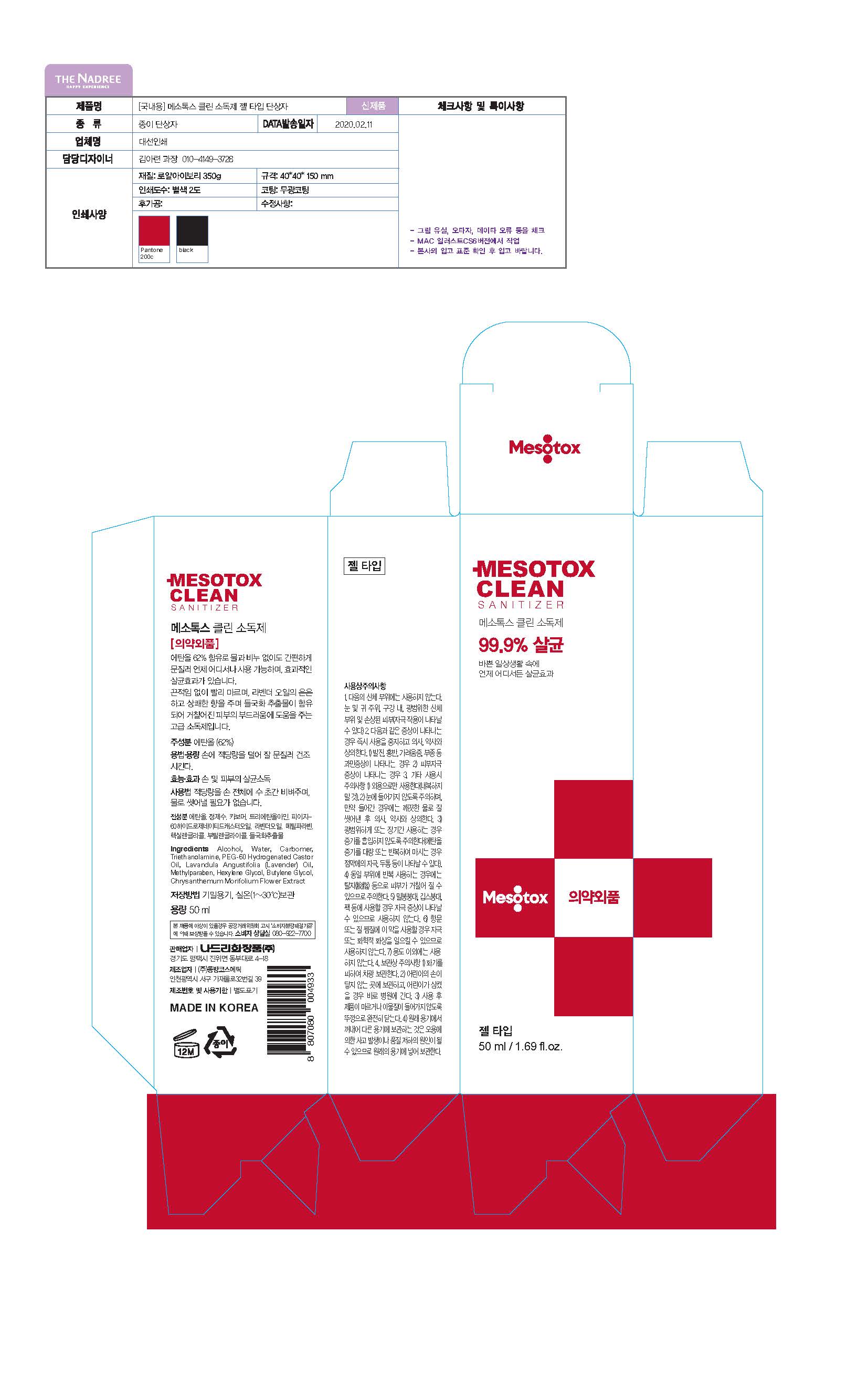 DRUG LABEL: MESOTOX CLEAN SANITIZER
NDC: 74442-0008 | Form: GEL
Manufacturer: THE NADREE Co., Ltd.
Category: otc | Type: HUMAN OTC DRUG LABEL
Date: 20211105

ACTIVE INGREDIENTS: ALCOHOL 62 g/100 mL
INACTIVE INGREDIENTS: BUTYLENE GLYCOL; WATER

Drug Facts

ACTIVE INGREDIENT

Alcohol 62%

INACTIVE INGREDIENT

Water, Carbomer, Triethanolamine, Polyoxyethylene Hydrogenated Castor Oil, Lavandula Angustifolia (Lavender) Oil, Methylparaben, Butylene Glycol, Hexylene Glycol, Chrysanthemum Morifolium Flower Extract

PURPOSE

Antiseptic

KEEP OUT OF REACH OF THE CHILDREN

INDICATIONS AND USAGE

For the external use only

WARNINGS

For external use only.

Flammable, keep away from fire or flame.

When using this product keep out of eyes. If contact with eyes occurs, rinse promptly and thoroughly with water.

Stop use and ask a doctor if significant irritation or sensitization develops.

Keep out of reach of children. If swallowed, get medical help or contact a Poison Control Center right away.

DOSAGE AND ADMINISTRATION

Put suitable amount in your palm to cover hands and rub hands together briskly until dry.